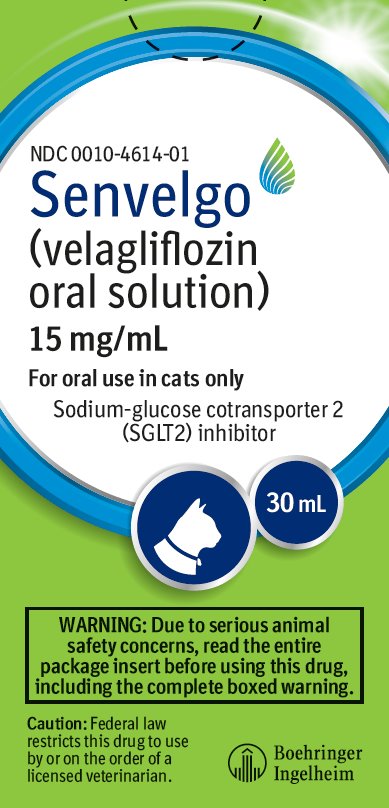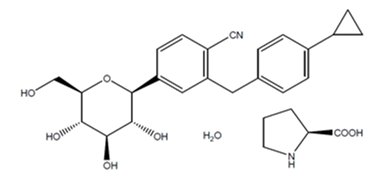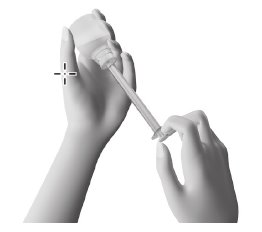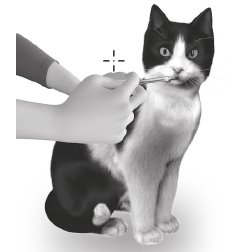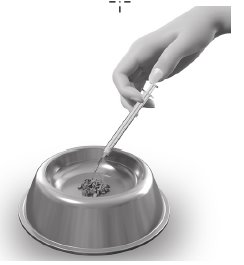 DRUG LABEL: Senvelgo
NDC: 0010-4614 | Form: SOLUTION
Manufacturer: Boehringer Ingelheim Animal Health USA Inc.
Category: animal | Type: PRESCRIPTION ANIMAL DRUG LABEL
Date: 20240424

ACTIVE INGREDIENTS: VELAGLIFLOZIN PROLINE 15 mg/1 mL
INACTIVE INGREDIENTS: PROPYLENE GLYCOL; ALCOHOL

Senvelgo®
(velagliflozin oral solution)

15 mg/mL

For oral use in cats only

Sodium-glucose cotransporter 2 (SGLT2) inhibitor

Caution:

Federal law restricts this drug to use by or on the order of a licensed veterinarian.

WARNING: DIABETIC KETOACIDOSIS/EUGLYCEMIC DIABETIC KETOACIDOSIS

- Cats treated with SENVELGO may be at an increased risk of diabetic ketoacidosis or euglycemic ketoacidosis (see Adverse Reactions). As diabetic ketoacidosis and euglycemic ketoacidosis in cats treated with SENVELGO may result in death, development of these conditions should be treated promptly, including insulin administration and discontinuation of SENVELGO (see Monitoring).
- Due to the risk of developing diabetic ketoacidosis or euglycemic ketoacidosis, do not use SENVELGO in cats with diabetes mellitus who have previously been treated with insulin, who are receiving insulin, or in cats with insulin-dependent diabetes mellitus (see Contraindications).
- SENVELGO should not be initiated in cats with anorexia, dehydration, or lethargy at the time of diagnosis of diabetes mellitus or without appropriate screening tests (see Animal Safety Warnings).

Description:

SENVELGO® (velagliflozin oral solution) equal to velagliflozin L-proline H2O 20.051 mg/mL, is a clear, colorless to slightly yellow, to slightly brown, liquid multi-dose preparation consisting of 1.5% w/v velagliflozin in an aqueous mixture of propylene glycol and ethanol intended for oral use in cats. SENVELGO is an orally active, sodium-glucose cotransporter 2 (SGLT2) inhibitor.

The chemical name of velagliflozin is 2-(4-cyclopropyl-benzyl)-4-((2S,3R,4R,5S,6R)-3,4,5-trihydroxy-6-hydroxymethyltetrahydropyran-2-yl)-benzonitrile. It forms a co-crystal with L-proline ((S)-pyrrolidine-2-carboxylic acid) as a monohydrate and velagliflozin, L-proline and H2O are in 1:1:1 ratios. Its empirical formula is C23H25NO5 x C5H9NO2 x H2O, its molecular formula is C28H36N2O8, and its structural formula is:

Indication:

SENVELGO is indicated to improve glycemic control in otherwise healthy cats with diabetes mellitus not previously treated with insulin.

Dosage and Administration:

Always provide the Client Information Sheet with each prescription.

Dosing instructions:

The SENVELGO dose is 0.45 mg/lb of body weight (1 mg/kg), once daily regardless of blood glucose level. The dose may be administered directly into the mouth or with a small amount of wet food. Do not mix into food. The solution should be given at approximately the same time every day. If a dose is missed, it should be given as soon as possible on the same day. If the cat vomits within 30 minutes of dosing, the dose can be repeated.

SENVELGO should be administered using the dosing syringe provided in the package. The dosing syringe fits onto the bottle and has a body weight scale with increments per pound of body weight. The dose should be rounded down to the nearest pound. After administration, close the bottle tightly with the cap. If needed, the syringe can be cleaned with a clean, dry cloth.

Prior to initiation of treatment:

Prior to initiation of SENVELGO, the veterinarian should ensure the cat is alert, active, eating, and drinking. The veterinarian should conduct a physical examination, obtain a medical history, CBC, serum chemistry, serum fructosamine, and urinalysis including evaluation for ketonuria (see Animal Safety Warnings).

If there is a delay of more than a week between diagnosis of diabetes mellitus and initiation of SENVELGO, the veterinarian should re-evaluate the cat with a full physical examination and updated history to ensure the cat still meets the criteria described above. A delay of more than a week between diagnosis and starting SENVELGO may increase the risk of developing diabetic ketoacidosis.

Monitoring of cats receiving SENVELGO:

Sudden onset of hyporexia/anorexia, lethargy, dehydration, or weight loss in cats receiving SENVELGO should prompt immediate discontinuation of SENVELGO and assessment of diabetic ketoacidosis, regardless of blood glucose level.

Evaluate for ketonuria 2 to 3 days after initiation of treatment and approximately 7 days after initiation of treatment and anytime the cat shows signs of illness.If ketonuria is present, discontinue SENVELGO and promptly treat with insulin, even if blood glucose is normal.

During the first 4 weeks after initiation of SENVELGO, glycemic control and clinical improvement should be evaluated.

- A physical examination, blood glucose curve, serum fructosamine, and body weight should be assessed at 1 and 4 weeks after initiating SENVELGO.
- SENVELGO should be discontinued, and initiation of insulin considered, in cats demonstrating poor glycemic control (weight loss, average blood glucose from a glucose curve > 300 mg/dL or fructosamine values suggesting poor control (> 450 µmol/L) after 4 weeks of treatment.

During ongoing treatment with SENVELGO, blood glucose, fructosamine, urinary ketones, serum chemistry, body weight, hydration status, and clinical signs of diabetes mellitus should be routinely monitored.

- Presence of ketonuria should prompt discontinuation of SENVELGO and transition to insulin.
- Cats with increasing or persistently elevated triglyceride or cholesterol levels may have declining glycemic control or pancreatitis, and may be at risk of developing diabetic ketoacidosis or euglycemic diabetic ketoacidosis (diabetic ketoacidosis with normal blood glucose levels). Consider further evaluation and discontinuation of SENVELGO in these cats.
- Increasing or persistently elevated feline pancreas-specific lipase (fPL) should prompt further evaluation for pancreatitis and consideration of discontinuation of SENVELGO.

- Initial mild weight loss may be seen with SENVELGO associated with its mode of action (glucosuria and caloric wasting). Unintentional weight loss which doesn’t improve or stabilize within 7 days may indicate the need to evaluate for concurrent disease and consideration of discontinuation of SENVELGO (see Adverse Reactions).
- If clinical signs of illness occur, evaluate the cat as soon as possible to ensure it is not at risk for diabetic ketoacidosis or euglycemic diabetic ketoacidosis (see Animal Safety Warnings).
- SENVELGO should be discontinued if the cat’s clinical condition declines and/or glycemic control worsens after initial improvement.

Cats may present with diabetic ketoacidosis and a normal blood glucose concentration (euglycemic diabetic ketoacidosis). Delay in recognition and treatment of diabetic ketoacidosis and euglycemic diabetic ketoacidosis may result in increased morbidity and mortality.

Development of diabetic ketoacidosis or euglycemic ketoacidosis requires the following actions:

- Discontinuation of SENVELGO
- Prompt initiation of insulin therapy
- Administration of dextrose or other carbohydrate source, regardless of blood glucose concentration
- Appropriate nutritional support should be promptly initiated to prevent or treat hepatic lipidosis.

Contraindications:

Do not use SENVELGO in cats with diabetes mellitus who have previously been treated with insulin, who are receiving insulin, or in cats with insulin-dependent diabetes mellitus. The use of SENVELGO in cats with insulin-dependent diabetes mellitus, or the withdrawal of insulin and initiation of SENVELGO, is associated with an increased risk of diabetic ketoacidosis or euglycemic diabetic ketoacidosis and death.

Warnings:

User Safety Warnings: Not for use in humans.Keep out of reach of children.

Wash hands after use. This product may cause mild eye irritation. Avoid contact with eyes. If the product accidentally gets into the eyes, rinse eyes immediately with plenty of water; if wearing contact lenses, rinse the eyes first then remove contact lens(es) and continue to rinse for 5-10 minutes. If eye irritation continues or accidental ingestion occurs, seek medical advice and provide this product information to the physician. Exposure to product may induce local or systemic allergic reaction in sensitized individuals. Oral exposure to velagliflozin may cause transient effects such as increased renal glucose excretion, increased urine volume, and hypoglycemia.

Animal Safety Warnings:

SENVELGO should not be initiated in cats with:

- Anorexia, dehydration, or lethargy at the time of diagnosis of diabetes mellitus as it may indicate the presence of other concurrent disease and increase the risk of diabetic ketoacidosis.
- Ketonuria, ketonemia, or suspected diabetic ketoacidosis or a history of the same
- Clinical suspicion of pancreatitis within the last month based on clinical signs, serum fPL > 12 mcg/L, and/or diagnostic imaging consistent with pancreatitis.
- Chronic or unresponsive diarrhea
- Cachexia
- Bilirubin > 0.5 mg/dL
- Creatinine > 2 mg/dL

SENVELGO may cause a mild increase in serum creatinine, blood urea nitrogen (BUN), phosphorus, and sodium in cats with or without chronic kidney disease within weeks of starting therapy, followed by a stabilization of values.

Cats with baseline creatinine between 1.6 and 2 mg/dL when SENVELGO treatment is started should be closely monitored for signs of volume depletion/dehydration and body weight loss. Renal function should be monitored within the first week of treatment initiation and then according to standard chronic kidney disease guidelines. SENVELGO has not been evaluated in cats with baseline creatinine > 2 mg/dL.

Cats should be screened for urinary tract infections and treated, if indicated, when initiating SENVELGO. Cats treated with SENVELGO should be monitored for urinary tract infections and treated promptly.

Cats should be evaluated for concurrent disease including pancreatitis, infectious disease, urinary tract infection, neoplasia, and hypersomatotropism (acromegaly) before initiating and while receiving SENVELGO as these conditions may increase the risk of developing diabetic ketoacidosis.

Persistently low or worsening serum chloride values compared to the pre-treatment value may indicate the development of diabetic ketoacidosis or euglycemic diabetic ketoacidosis.

SENVELGO may cause increased serum calcium and persistent elevations may require additional diagnostics. Persistent elevated calcium has been associated with increased risk of calcium-containing urolith formation in other SGLT2 inhibitors.

Cats should be closely monitored for development of diabetic ketoacidosis or euglycemic diabetic ketoacidosis (for example, ketonuria or anorexia) after stopping SENVELGO. Euglycemia may persist for 2 to 3 days after stopping SENVELGO.

Keep SENVELGO in a secure location out of reach of dogs, cats, and other animals to avoid accidental ingestion or overdose.

Precautions:

Consider temporarily discontinuing SENVELGO during times of decreased caloric intake, such as surgery or decreased appetite, as continued administration of SENVELGO may increase the risk of diabetic ketoacidosis.

SENVELGO contains propylene glycol. When cats are administered SENVELGO at the 1 mg/kg/day dose, cats receive 40 mg/kg/day of propylene glycol. Exceeding 80 mg/kg/day of propylene glycol may result in excess hepatic glycogen stores. Use caution when administering SENVELGO to cats receiving other products that contain propylene glycol.

Glucosuria may persist for 2-3 days after stopping SENVELGO. In cats receiving SENVELGO, glucosuria is not a reliable indicator for monitoring glycemic control.

The safety and effectiveness of SENVELGO has not been evaluated in cats with chronic kidney disease (IRIS (International Renal Interest Society) Stages 3 and 4).

The concurrent use of volume depleting drugs in cats treated with SENVELGO has not been evaluated.

SENVELGO has not been evaluated with concurrent use of insulin or other blood glucose lowering treatments.

The safety and effectiveness of SENVELGO in breeding, pregnant, and lactating cats has not been evaluated.

Adverse Reactions:

Two hundred fifty-two (252) cats with diabetes mellitus were enrolled in a 180-day multicenter field study. Safety data were evaluated in 252 cats treated with at least one dose of SENVELGO. Regardless of blood glucose level, cats received SENVELGO at a dose of 0.45 mg/lb once daily.

The most common adverse reactions were diarrhea or loose stool, weight loss, vomiting, polyuria, polydipsia, and elevated blood urea nitrogen (BUN). The table below summarizes the adverse reactions reported in the study.

Adverse Reactions | Frequency (N=252); Number (%)
Diarrhea (including loose stool) | 132 (52.3%)
Weight loss* | 111 (44%)
Vomiting | 92 (36.5%)
Polyuria | 46 (18.3%)
Polydipsia | 42 (16.7%)
BUN† | 39 (15.5%)
Anorexia or hyporexia | 34 (13.5%)
Hypersalivation and/or gagging | 33 (13.1%)
Urine specific gravity > 1.060 | 29 (11.5%)
Dehydration | 28 (11.1%)
Lethargy | 20 (7.9%)
Polyphagia | 19 (7.5%)
Urinary tract infections/cystitis | 18 (7.1%)
Diabetic ketoacidosis or euglycemic diabetic ketoacidosis‡ | 18 (7.1%)
Hypercalcemia | 16 (6.3%)
Ketonuria§ | 14 (5.6%)
Inappropriate urination | 14 (5.6%)
Death or euthanasia | 13 (5.2%)
Elevated AST and/or ALT** | 12 (4.8%)
Hypertriglyceridemia†† | 12 (4.8%)
Hyperphosphatemia | 12 (4.8%)
Elevated fPL | 11 (4.4%)
Pancreatitis | 10 (4.0%)
Elevated creatinine | 9 (3.6%)
Hepatic lipidosis | 6 (2.4%)
Urinary incontinence | 3 (1.2%)

*Approximately 80 cats had weight loss during the first week of treatment, likely due to dehydration and/or caloric wasting from glucosuria.
†Most cats had elevations ≤ 1.5X upper limit of normal (ULN).
‡All but 5 cases occurred within 2 weeks of starting SENVELGO.Twelve of these cats had euglycemic diabetic ketoacidosis.
§These cats did not progress to diabetic ketoacidosis and all but one developed ketonuria within a week of starting SENVELGO. The cats discontinued SENVELGO and transitioned to insulin.
**Four of these cats had AST (aspartate aminotransferase) and/or ALT (alanine aminotransferase) > 2X ULN.
††These cats sometimes also had elevated cholesterol.

The following adverse reactions were seen in the study with < 1% frequency: elevated creatine kinase (> 3X ULN), hypoglycemia without clinical signs (glucose ≤ 50 mg/dL), anemia, abnormal behavior, bradycardia, and dermatitis.

Ketonuria and diabetic ketoacidosis: Thirty-two (32) cats developed ketonuria, diabetic ketoacidosis or euglycemic diabetic ketoacidosis and were removed from the study. Twenty-six (26) of these cats developed ketonuria, diabetic ketoacidosis, or euglycemic diabetic ketoacidosis within the first 7 days of treatment with SENVELGO. Thirteen (13) of these cats developed ketonuria without further progression to diabetic ketoacidosis or euglycemic ketoacidosis and transitioned to insulin. An additional thirteen (13) cats developed diabetic ketoacidosis or euglycemic ketoacidosis. Nine cats recovered after hospitalization and intensive treatment. Three of the 9 cats had concurrent conditions: hepatopathy (1), hepatic lipidosis (1), and pancreatitis and hepatic lipidosis (1). Four of the 13 cats were euthanized; three because the owners declined treatment and one cat was euthanized after not responding to hospitalization and intensive treatment.

Six cats developed ketonuria, diabetic ketoacidosis or euglycemic diabetic ketoacidosis after the first 7 days of treatment. One cat developed ketonuria without progression to diabetic ketoacidosis or euglycemic ketoacidosis after more than 4 months on SENVELGO. Five cats developed diabetic ketoacidosis or euglycemic ketoacidosis. Two cats (one with concurrent pancreatitis and hepatic lipidosis) were treated and recovered. One with concurrent pancreatitis was treated and recovered but died several days later. Two of the five cats were euthanized; one cat was euthanized after poor response to hospitalization and intensive therapy; and one was euthanized due to declining condition unrelated to diabetic ketoacidosis.

Thirty-eight enrolled cats had been previously treated with insulin. Of those 38 cats, 12 (32%) developed ketonuria, diabetic ketoacidosis, or euglycemic diabetic ketoacidosis during the first week and were removed from the study. These 12 cats are included in the 26 cases reported above and represent 46% of the cases removed in the first week of treatment due to ketonuria or ketoacidosis.

Death and euthanasia: Nineteen cats died (3) or were euthanized (16) during the study, or shortly following removal from the study, with thirteen possibly related to SENVELGO use or declining glycemic control. In addition to 6 of the cases associated with diabetic ketoacidosis described above, euthanasia was associated with the following conditions (number of cats): acute renal failure within a week of starting SENVELGO (1), worsening or emergent urinary incontinence associated with poor glycemic control (2), worsening polyuria/polydipsia and inappropriate urination (1), progressive signs of diabetes mellitus (1), declining condition and suspected pancreatitis (1), azotemia and lack of effect within a week of starting SENVELGO and possible concurrent hypersomatotropism (1).

Contact Information:

To report suspected adverse drug events, for technical assistance, or to obtain a copy of the Safety Data Sheet (SDS), contact Boehringer Ingelheim Animal Health at 1-888-637-4251. For additional information about adverse drug experience reporting for animal drugs, contact FDA at 1-888-FDA-VETS or online at www.fda.gov/reportanimalae.

Information for Cat Owners:

Please provide and review the Client Information Sheet with cat owners to ensure they understand the entire contents before SENVELGO is administered. The Client Information Sheet contains important information regarding the use of SENVELGO. Owners should be advised to discontinue SENVELGO and contact a veterinarian immediately if their cat develops anorexia, lethargy, vomiting, diarrhea, or weakness.

Clinical Pharmacology:

Mechanism of Action:

Velagliflozin is an inhibitor of sodium-glucose cotransporter 2 (SGLT2), the renal transporter responsible for reabsorption of glucose from the glomerular filtrate back into the circulation. By inhibiting SGLT2, velagliflozin reduces the reabsorption of filtered glucose and lowers the renal threshold for glucose, thereby increasing urinary glucose excretion.

Pharmacokinetics: In a laboratory study conducted to determine the prandial state of maximum exposure,systemic exposure for velagliflozin was greater in the fasted state than in the fed state by170% for the mean maximum observed plasma concentration (Cmax), and by 45% for the mean area under the plasma concentration versus time curve (AUC) from dosing (time 0) to the last quantifiable concentration (AUC0-last), respectively.

In a well-controlled, laboratory margin of safety study in healthy, adult cats (see Target Animal Safety), after repeat daily oral dosing for six months, a slight to moderate increase in exposure to velagliflozin was observed. In addition, a tendency for a less than dose proportionalincrease of maximum plasma concentration (Cmax) and exposure (AUC) over the tested dose range was noted.

Following oral administration of SENVELGO in cats at 1 mg/kg, velagliflozin was rapidly absorbed with a median time to maximum concentration of 0.25 hours. The velagliflozin mean (± standard deviation) Cmax was 1030 (± 361) ng/mL and the mean AUC0-last to the last quantifiable plasma concentration was 3295 (± 1098) day*ng/mL. The elimination half-life of velagliflozin was 3.68 (± 0.34) hours.

Effectiveness

Two hundred and fifty-two (252) cats diagnosed with diabetes mellitus were enrolled in a 180-day multicenter field study. The cats included various purebred and mixed breed cats ranging in age from 4 to 18 years and in weight from 5.7 to 26.5 lbs (2.6 to 12 kg). Cats were administered SENVELGO at a dose of 0.45 mg/lb (1 mg/kg) orally, once daily, regardless of blood glucose level, beginning on Day 0. Cats were evaluated at Days 2 or 3, and Days 7 and 30 and then monthly.

Treatment success was evaluated on Day 30 and was defined as improvement in at least one clinical sign of diabetes mellitus (polyuria, polydipsia, unintended weight loss, polyphagia, or diabetic neuropathy) and improvement in at least one blood glucose variable (blood glucose curve mean or serum fructosamine).

Of 198 cats included in the effectiveness-evaluable population:

- 175 cats (88.4%) were considered a treatment success on Day 30 (lower bound of the two-sided 90% confidence interval was 84%).
- Mean blood glucose decreased from 446.4 mg/dL (single fasted sample) prior to Day 0 to 169.8 mg/dL (blood glucose curve mean) on Day 30
- Mean fructosamine levels decreased from 551.4 µmol/L prior to Day 0 to 332.0 µmol/L on Day 30.
- Improvements in the clinical signs of polyuria, polydipsia, body weight, polyphagia, and diabetic neuropathy on Day 30 were observed in 125/177 (71%), 128/176 (73%), 133/167 (80%), 33/80 (41%), and 7/30 cats (23%), respectively.
- 157 cats completed the 180-day study

Target Animal Safety:

In a well-controlled laboratory margin of safety study, SENVELGO was administered orally to fasted, healthy, 8 to 9 month old cats at 0, 1, 3, or 5 mg/kg body weight(corresponding to 1X, 3X or 5X the intended labeled point dose of 1 mg/kg) once daily for26 weeks (6 months). Control cats (0 mg/kg) received saline at a volume equal to the 5 mg/kg dose. There were eight cats per group (4 females, 4 males). All cats survived the study and there were no SENVELGO-related effects on ophthalmic examinations, indirect systolic blood pressure measurements, and blood coagulation parameters. Hypersalivation and vomiting after dose administration occurred infrequently and was only observed in the groups that received SENVELGO.

During physical examinations on Days 14 and 28, there was a drug-related decrease in heart rate (< 140 bpm) in the cats that received SENVELGO compared to the control cats. There were no other drug-related effects on physical examinations.

Polydipsia, glucosuria, decreased urine creatinine, and diarrhea were reported more frequently in cats that received SENVELGO than in control cats.

Reddish, mucoid feces were observed in three instances in the 1X group cats. One cat in the 5X group had decreased activity, vomiting, and reduced feed consumption for one day, and reddened rectal mucous membranes were observed over the next 5 days. Two cats (3X and 5X groups) were each observed to have a reddened prepuce with white-yellow discharge twice during the study that was not associated with abnormal urinalyses.

Food consumption was higher in the cats that received SENVELGO compared to the control cats. The rate of body weight gain was lower in the 5X group cats compared to cats in the control, 1X and 3X groups.

There were drug-related increases in reticulocyte count, mean corpuscular hemoglobin, mean corpuscular volume, and Heinz body percentage, and a decrease in mean corpuscular hemoglobin concentration in the cats that received SENVELGO compared to control cats. None of the cats showed any clinical signs of anemia and the number of erythrocytes, hemoglobin, and hematocrit values were normal. There was no effect of SENVELGO on white blood cells and platelets.

There were drug-related increases in serum magnesium, albumin, cholesterol, and triglycerides in the cats that received SENVELGO, with some magnesium, serum albumin and triglyceride values above the reference range. There was a drug-related decrease in mean BUN in the cats that received SENVELGO. There were no other treatment-related changes in serum chemistry parameters, including serum glucose and symmetric dimethylarginine (SDMA).

A reticular pattern was observed on the surface of the liver of one control, three 1X, four 3X, and three 5X group cats.

How Supplied:

SENVELGO (velagliflozin oral solution) 15 mg/mL is available in nominal fill volumes of 12 mL and 30 mL and supplied in plastic bottles of 35 mL and 45 mL respectively, with a dosing syringe.

NDC 0010-4614-01 – 30 mL

NDC 0010-4614-02 – 12 mL

Storage Information:

SENVELGO can be stored at or below 77°F (25°C) with excursions permitted up to 104°F (40°C). Once the bottle is opened, use the contents within six months.

Approved by FDA under NADA # 141-568

Marketed by:

Boehringer Ingelheim Animal Health USA Inc.

Duluth, GA 30096

SENVELGO® is a registered trademark of Boehringer Ingelheim Vetmedica GmbH, used under license.

© 2024 Boehringer Ingelheim Animal Health USA Inc. All rights reserved.

Revised 03/2024

L65280324

Client Information Sheet

Senvelgo®

(velagliflozin oral solution)

15 mg/mL

For oral use in cats only

Sodium-glucose cotransporter 2 (SGLT2) inhibitor

The Client Information Sheet contains important information about SENVELGO® (velagliflozin oral solution). You should read this information before you start giving SENVELGO to your cat and review it each time the prescription is refilled as there may be new information. This sheet is provided only as a summary and does not take the place of instructions from your veterinarian. Talk with your veterinarian if you do not understand any of this information or if you want to know more about SENVELGO.

What is SENVELGO?

SENVELGO is a drug used to lower high blood glucose (sugar) in otherwise healthy cats with diabetes mellitus not previously treated with insulin. SENVELGO causes sugar to be passed in the urine by preventing the kidneys from pulling sugar back into the blood.

What is diabetes mellitus (commonly called diabetes)?

Diabetes happens when a cat does not make enough insulin (insulin dependent), or the cat’s cells do not react correctly to insulin (insulin resistant). Some cats may begin as insulin resistant but may slowly become insulin dependent over time. Sugar is an important source of energy for the cells in your cat’s body. Cats with diabetes have high blood sugar (hyperglycemia) because the sugar cannot get into the cells to be used for energy. Insulin helps sugar get into your cat’s cells for energy. There is no test available for your veterinarian to know if your cat makes enough insulin or not. Cats with diabetes may show an increased thirst, urination, and hunger; weight loss; and/or weakness in the back legs. Cats who are insulin dependent should not be treated with SENVELGO because it can cause serious, sometimes fatal, side effects.

What are some of the possible side effects of SENVELGO?

SENVELGO may be associated with side effects. Serious side effects have happened with or without warning and sometimes led to death in cats treated with SENVELGO. Serious side effects may require your cat to be hospitalized and to be given specific treatments, including insulin. The most common side effects are diarrhea or loose stool, vomiting, and weight loss.

STOP SENVELGO AND CONTACT YOUR VETERINARIAN IMMEDIATELY IF YOU NOTICE ANY OF THE FOLLOWING CHANGES OR SIDE EFFECTS IN YOUR CAT:

- Less interest in food or not eating
- Lack of energy or change in normal activity
- Vomiting or diarrhea
- Weakness, difficulty walking or standing

What should I discuss with my veterinarian before giving SENVELGO?

Tell your veterinarian if:

- Your cat is currently or was previously treated with insulin or other anti-diabetic medications.
- Your cat has been previously diagnosed with diabetic ketoacidosis (a buildup of acids in the blood) or liver or kidney disease.
- Your cat has any other serious health conditions such as acute vomiting, diarrhea, decreased appetite, or weight loss.
- Your cat is taking other medications including prescription drugs and over-the-counter medication.
- Your cat is pregnant, nursing, or you intend to breed him/her.
- Your cat has any planned procedures that involve anesthesia, such as surgery or dentistry.

When should I take my cat to the veterinarian?

- It is very important to take your cat to the veterinarian twice during the first week of taking SENVELGO to monitor your cat for side effects even if your cat seems fine. Your cat should be examined by your veterinarian 2 or 3 days after starting SENVELGO and again about 7 days after starting SENVELGO.
- It is also important to take your cat to the veterinarian immediately if your cat is showing signs of illness including decreased appetite or decreased thirst, vomiting, weakness, decreased activity or depressed attitude.
- It is important to discuss your cat’s response to SENVELGO at regular checkups.
- Your veterinarian will determine if your cat is responding as expected and whether your cat should continue using SENVELGO.

What kind of results can I expect when my cat is on SENVELGO for diabetes mellitus?

You may see a decrease in the amount of thirst, urine, and hunger in your cat.

How do I give SENVELGO to my cat?

SENVELGO should be given directly into your cat’s mouth with the provided dosing syringe or placed on a small amount of wet food your cat will eat completely (approximately 1 to 3 teaspoons of food). The dosing syringe fits into the bottle opening and has a body weight scale to use for measuring the dose. The body weight scale on the syringe is made to give the amount of SENVELGO prescribed by your veterinarian.

Follow your veterinarian’s instructions for how much and how often to give SENVELGO.

- Remove the cap from the bottle and gently push the end of the dosing syringe into the bottle opening.
- Turn the bottle/syringe upside down.
- Pull the plunger back and ﬁll the dosing syringe to the dose prescribed by your veterinarian.
- Turn the bottle upright and remove the dosing syringe from the bottle.

- Put the end of the dosing syringe into your cat’s mouth and push the plunger to give the dose.

- Or put the dose next to or on top of a small amount of wet food. Do not mix into food. If SENVELGO is put onto food, make sure your cat eats the food and the entire dose.

If your cat vomits within 30 minutes of giving the SENVELGO dose, your cat can be given the same dose again. If your cat vomits more than 30 minutes after giving SENVELGO, do not give SENVELGO again until the next scheduled dose. After dosing, replace the cap on the bottle and close tightly. If needed, the syringe can be cleaned with a clean, dry cloth.

What should I do if my cat gets more than the prescribed dose?

Contact your veterinarian if you see any side effects. If no side effects are seen, return to the dose prescribed by your veterinarian the following day.

What should I do if my cat gets less than the prescribed dose, or I miss a dose?

- If your cat gets less than the prescribed dose, return to the dose prescribed by your veterinarian the following day.
- If a dose is missed, it should be given as soon as possible on the same day.

How should I store SENVELGO?

SENVELGO can be stored at or below 77°F (25°C) with excursions permitted up to 104°F (40°C). Once the bottle is opened, use the contents within six months.

Keep SENVELGO in a secure location out of reach of dogs, cats, and other animals to avoid accidental ingestion or overdose.

Approved by FDA under NADA # 141-568

SENVELGO® is a registered trademark of Boehringer Ingelheim Vetmedica GmbH, used under license.

© 2024 Boehringer Ingelheim Animal Health USA Inc. All rights reserved.

Revised 03/2024